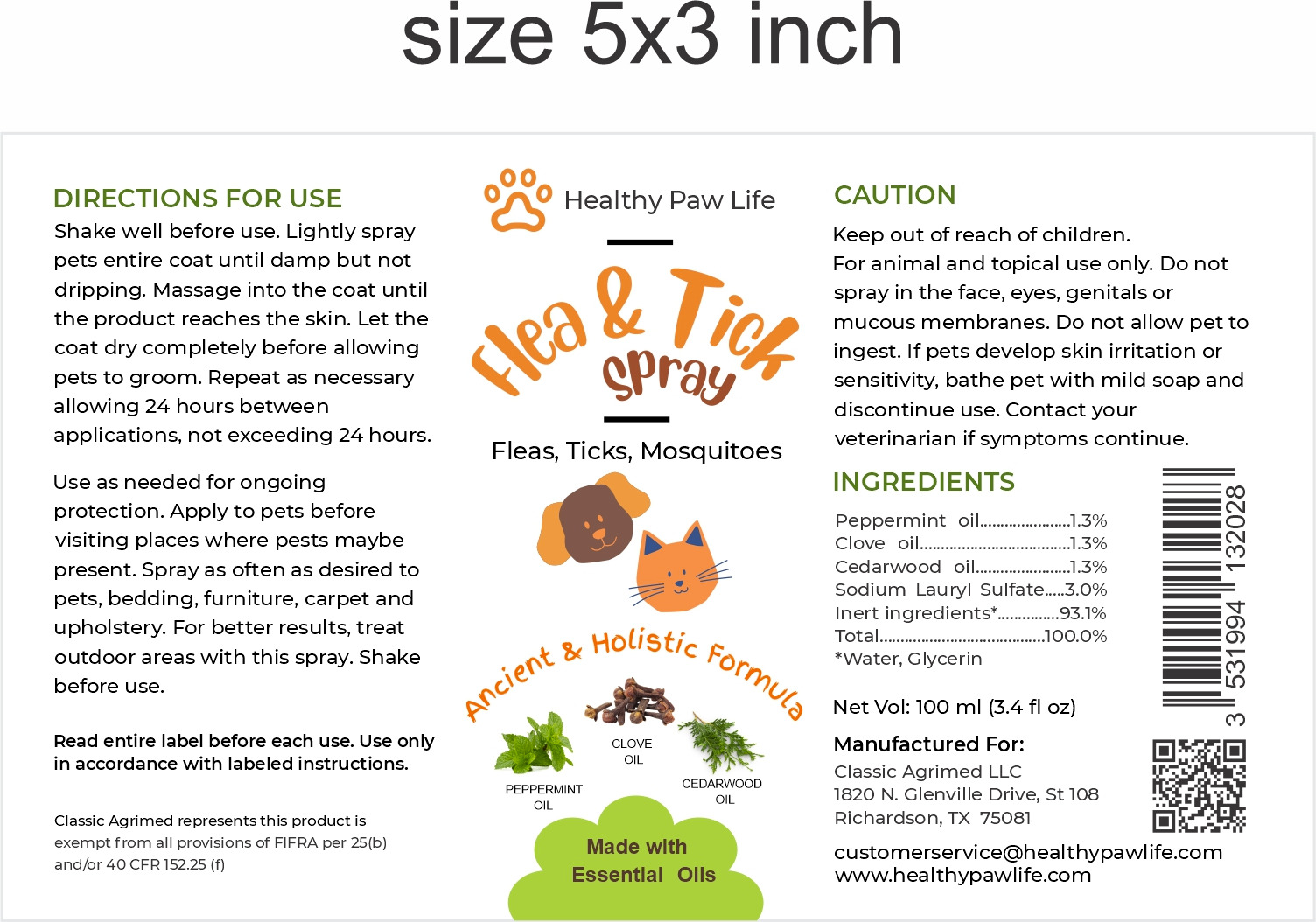 DRUG LABEL: HEALTHY PAW LIFE FLEA AND TICK
NDC: 86130-902 | Form: SPRAY
Manufacturer: CLASSIC AGRIMED LLC
Category: animal | Type: OTC ANIMAL DRUG LABEL
Date: 20231118

ACTIVE INGREDIENTS: PEPPERMINT OIL 1.3 g/100 mL; CEDAR LEAF OIL 1.3 g/100 mL; CLOVE OIL 1.3 g/100 mL
INACTIVE INGREDIENTS: SODIUM LAURYL SULFATE 3 g/100 mL

HEALTHY PAW LIFE FLEA & TICK SPRAY

Ingredients:
Peppermint oil................1.3%
clove Oll..................1.3%
Cedarwood oil..................1.3%
Sodium Lauryl Sulfate.....3.0%
Inert ingredients*.......93.1%
Total............100.0%
*Water, Glycerin

Description:
Lime Sulfur Spray for Hot Spot & Itch Relief for Dogs and Cats.

Directions For Use:
Shake well before use. Lightly spray pets entire coat until damp but not dripping. Massage into the coat until the product reaches the skin. Let the coat dry completely before allowing pets to groom. Repeat as necessary allowing 24 hours between applications, not exceeding 24 hours.
Use as needed for ongoing protection. Apply to pets before visiting places where pests maybe present. Spray as often as desired to pets, bedding, furniture, carpet and upholstery. For better results, treat outdoor areas with this spray. Shake before use.

Read entire label before each use. Use only in accordance with labeled instructions.

Caution:

Keep out of reach of children. For animal and topical use only. Do not spray in the face, eyes, genitals or mucous membranes. Do not allow pet to
ingest. If pets develop skin irritation or sensitivity, bathe pet with mild soap and discontinue use. Contact your veterinarian if symptoms continue.